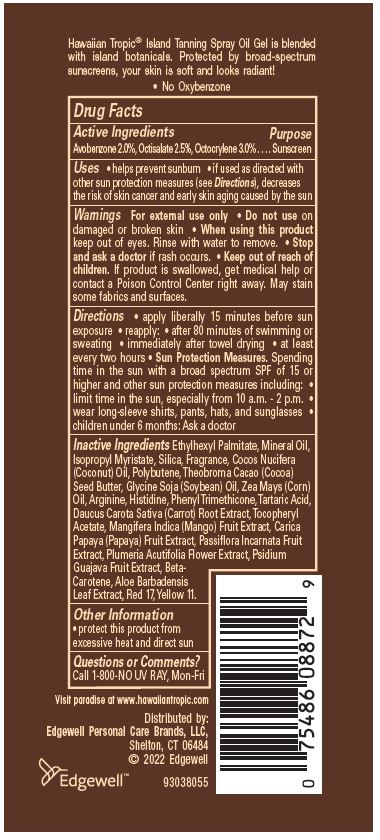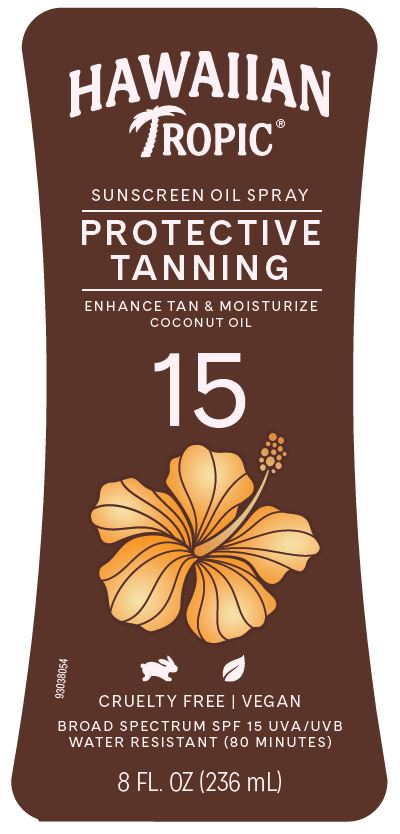 DRUG LABEL: HAWAIIAN TROPIC
NDC: 63354-319 | Form: OIL
Manufacturer: Edgewell Personal Care Brands LLC
Category: otc | Type: HUMAN OTC DRUG LABEL
Date: 20251021

ACTIVE INGREDIENTS: OCTISALATE 2.5 g/100 g; AVOBENZONE 2 g/100 g; OCTOCRYLENE 3 g/100 g
INACTIVE INGREDIENTS: ALOE VERA LEAF; D&C RED NO. 17; COCOA BUTTER; CORN OIL; POLYBUTENE (1400 MW); COCONUT OIL; TARTARIC ACID; CARROT; HISTIDINE; ETHYLHEXYL PALMITATE; D&C YELLOW NO. 11; PAPAYA; MINERAL OIL; PLUMERIA RUBRA FLOWER; PHENYL TRIMETHICONE; ALPHA-TOCOPHEROL ACETATE; PASSIFLORA INCARNATA FRUIT; SOYBEAN OIL; GLYCERYL OLEATE; BETA CAROTENE; GUAVA; MANGO; SILICON DIOXIDE; ARGININE; ISOPROPYL MYRISTATE

Active Ingredients

Avobenzone 2.0%, Octisalate 2.5%, Octocrylene 3.0%

Purpose

Sunscreen

Uses

• helps prevent sunburn • if used as directed with other sun protection measures (see Directions), decreases the risk of skin cancer and early skin aging caused by the sun

Warnings

For external use only

May stain some fabrics and surfaces.

Do not use on

damaged or broken skin

When using this product

keep out of eyes. Rinse with water to remove.

Stop and ask a doctor

if rash occurs.

Keep out of reach of children.

If product is swallowed, get medical help or contact a Poison Control Center right away.

Directions

• apply liberally 15 minutes before sun exposure • reapply: • after 80 minutes of swimming or sweating • immediately after towel drying • at least every two hours • Sun Protection Measures. Spending time in the sun with a broad spectrum SPF of 15 or higher and other sun protection measures including: • limit time in the sun, especially from 10 a.m. - 2 p.m. • wear long-sleeve shirts, pants, hats, and sunglasses • children under 6 months: Ask a doctor

Inactive Ingredients

Ethylhexyl Palmitate, Mineral Oil, Isopropyl Myristate, Silica, Fragrance, Cocos Nucifera (Coconut) Oil, Polybutene, Theobroma Cacao (Cocoa) Seed Butter, Glycine Soja (Soybean) Oil, Zea Mays (Corn) Oil, Arginine, Histidine, Phenyl Trimethicone, Tartaric Acid, Daucus Carota Sativa (Carrot) Root Extract, Tocopheryl Acetate, Mangifera Indica (Mango) Fruit Extract, Carica Papaya (Papaya) Fruit Extract, Passiflora Incarnata Fruit Extract, Plumeria Acutifolia Flower Extract, Psidium Guajava Fruit Extract, Beta-Carotene, Aloe Barbadensis Leaf Extract, Red 17, Yellow 11.

Other Information

• protect this product from excessive heat and direct sun

Questions or Comments?

Call 1-800-NO UV RAY, Mon-Fri

Principal Display Panel

HAWAIIAN
TROPIC®
SUNSCREEN OIL SPRAY
PROTECTIVE
TANNING
ENHANCE TAN & MOISTURIZE
COCONUT OIL
CRUELTY FREE | VEGAN
BROAD SPECTRUM SPF 15 UVA/UVB
WATER RESISTANT (80 MINUTES
8 FL. OZ (236 mL)